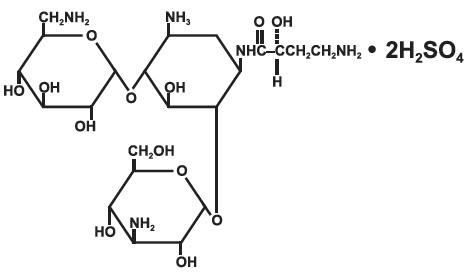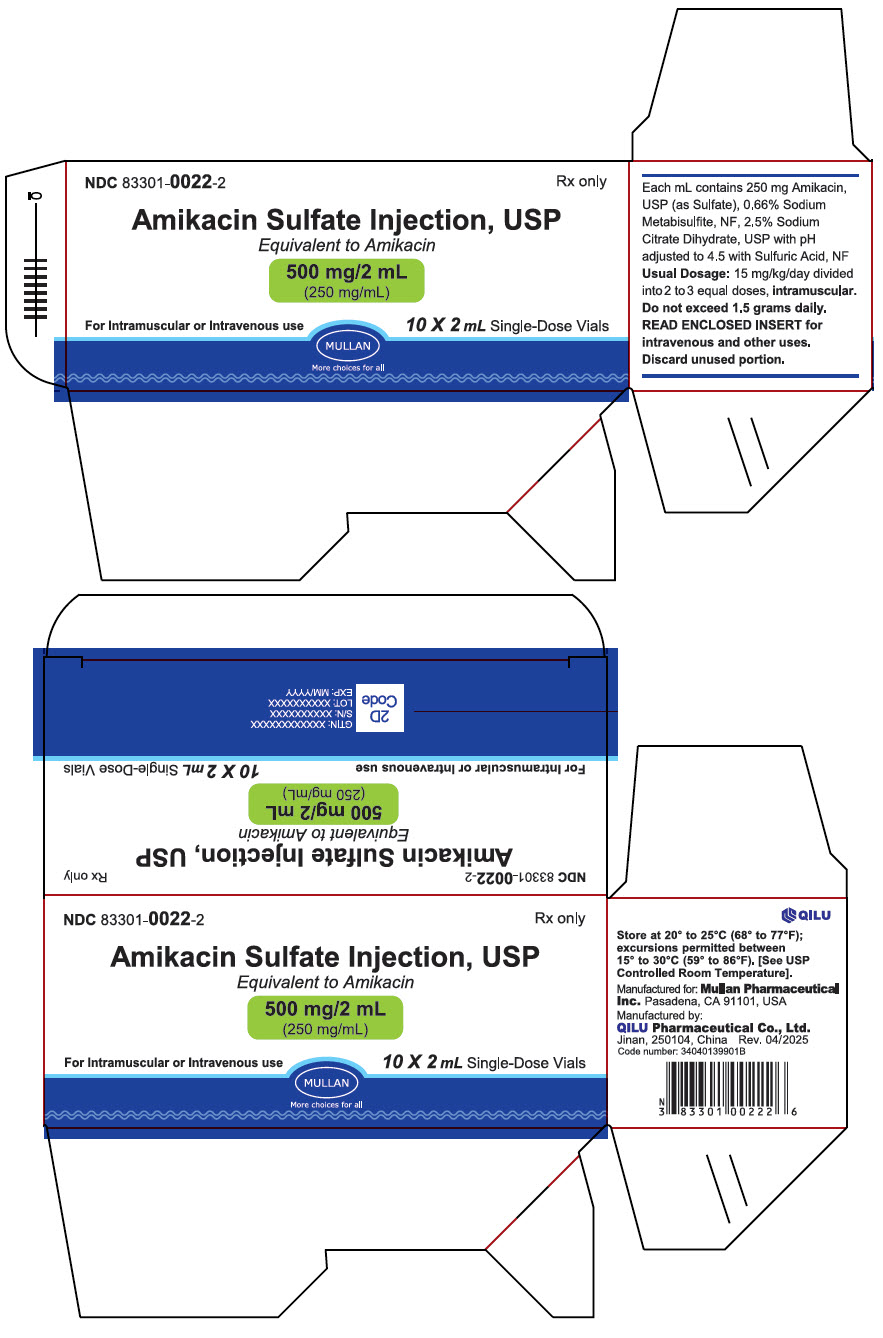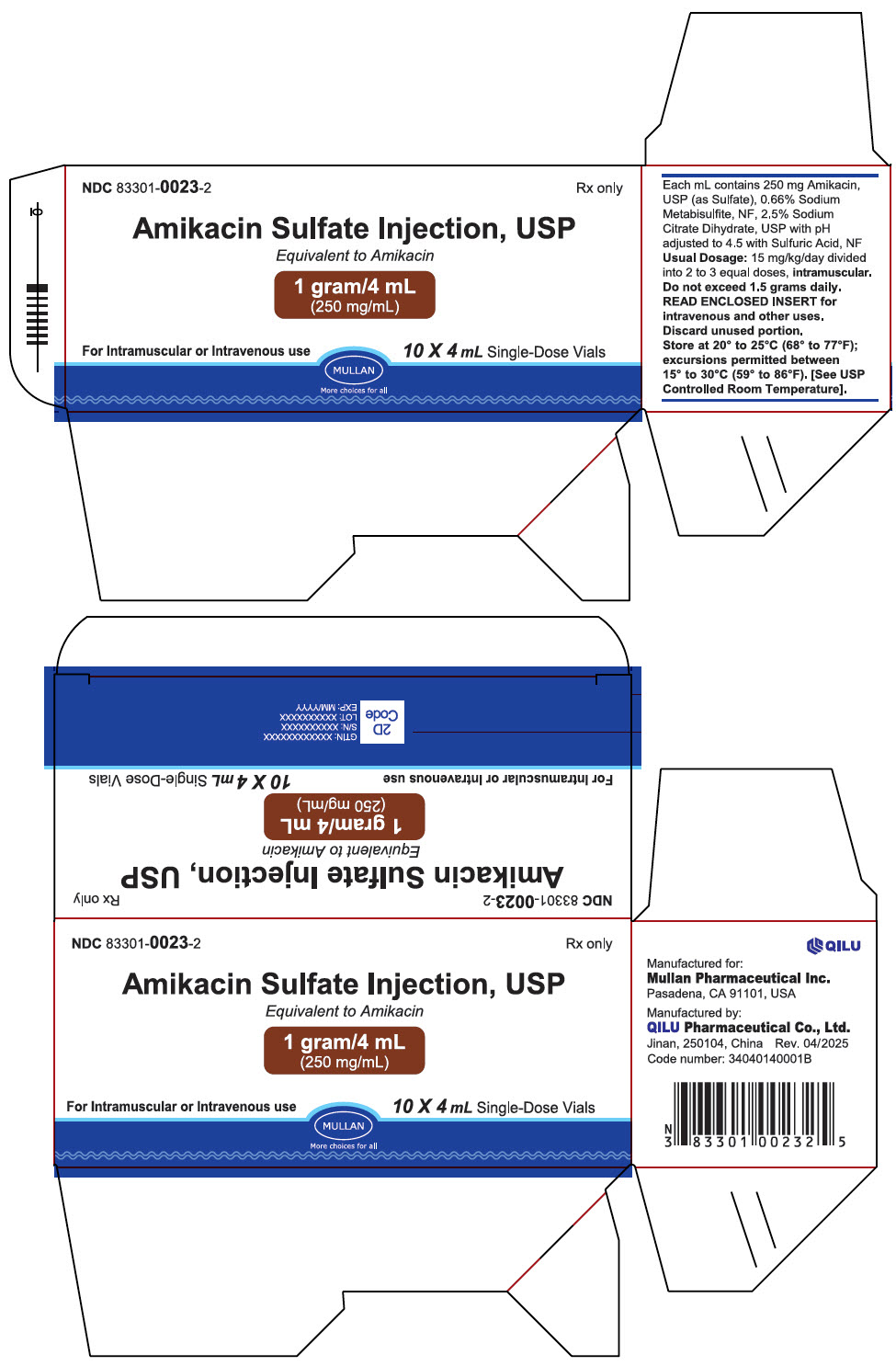 DRUG LABEL: Amikacin Sulfate
NDC: 83301-0022 | Form: INJECTION
Manufacturer: Mullan Pharmaceutical Inc.
Category: prescription | Type: HUMAN PRESCRIPTION DRUG LABEL
Date: 20260113

ACTIVE INGREDIENTS: AMIKACIN SULFATE 250 mg/1 mL
INACTIVE INGREDIENTS: SODIUM METABISULFITE; TRISODIUM CITRATE DIHYDRATE; SULFURIC ACID

Amikacin Sulfate Injection, USP

Rx only

To reduce the development of drug-resistant bacteria and maintain the effectiveness of the amikacin and other antibacterial drugs, amikacin should be used only to treat or prevent infections that are proven or strongly suspected to be caused by bacteria.

WARNINGS

Patients treated with parenteral aminoglycosides should be under close clinical observation because of the potential ototoxicity and nephrotoxicity associated with their use. Safety for treatment periods which are longer than 14 days has not been established.

Neurotoxicity, manifested as vestibular and permanent bilateral auditory ototoxicity, can occur in patients with preexisting renal damage and in patients with normal renal function treated at higher doses and/or for periods longer than those recommended. The risk of aminoglycoside-induced ototoxicity is greater in patients with renal damage. High frequency deafness usually occurs first and can be detected only by audiometric testing. Vertigo may occur and may be evidence of vestibular injury. Other manifestations of neurotoxicity may include numbness, skin tingling, muscle twitching and convulsions. The risk of hearing loss due to aminoglycosides increases with the degree of exposure to either high peak or high trough serum concentrations. Patients developing cochlear damage may not have symptoms during therapy to warn them of developing eighth-nerve toxicity, and total or partial irreversible bilateral deafness may occur after the drug has been discontinued. Aminoglycoside-induced ototoxicity is usually irreversible. Aminoglycosides are potentially nephrotoxic. The risk of nephrotoxicity is greater in patients with impaired renal function and in those who receive high doses or prolonged therapy.

Neuromuscular blockade and respiratory paralysis have been reported following parenteral injection, topical instillation (as in orthopedic and abdominal irrigation or in local treatment of empyema), and following oral use of aminoglycosides. The possibility of these phenomena should be considered if aminoglycosides are administered by any route, especially in patients receiving anesthetics, neuromuscular blocking agents such as tubocurarine, succinylcholine, decamethonium, or in patients receiving massive transfusions of citrate - anticoagulated blood. If blockage occurs, calcium salts may reverse these phenomena, but mechanical respiratory assistance may be necessary.

Renal and eighth-nerve function should be closely monitored especially in patients with known or suspected renal impairment at the onset of therapy and also in those whose renal function is initially normal but who develop signs of renal dysfunction during therapy. Serum concentrations of amikacin should be monitored when feasible to assure adequate levels and to avoid potentially toxic levels and prolonged peak concentrations above 35 micrograms per mL. Urine should be examined for decreased specific gravity, increased excretion of proteins, and the presence of cells or casts. Blood urea nitrogen, serum creatinine, or creatinine clearance should be measured periodically. Serial audiograms should be obtained where feasible in patients old enough to be tested, particularly high risk patients. Evidence of ototoxicity (dizziness, vertigo, tinnitus, roaring in the ears, and hearing loss) or nephrotoxicity requires discontinuation of the drug or dosage adjustment.

Concurrent and/or sequential systemic, oral or topical use of other neurotoxic or nephrotoxic products, particularly bacitracin, cisplatin, amphotericin B, cephaloridine, paromomycin, viomycin, polymyxin B, colistin, vancomycin, or other aminoglycosides should be avoided. Other factors that may increase risk of toxicity are advanced age and dehydration.

The concurrent use of amikacin with potent diuretics (ethacrynic acid, or furosemide) should be avoided since diuretics by themselves may cause ototoxicity. In addition, when administered intravenously, diuretics may enhance aminoglycoside toxicity by altering antibiotic concentrations in serum and tissue.

DESCRIPTION

Amikacin Sulfate Injection, USP is semi-synthetic aminoglycoside antibiotic derived from kanamycin. It is C22H43N5O13∙2H2SO4∙ O-3-amino-3-deoxy-α-D-glucopyranosyl-(1→4)- O-[6-amino-6-deoxy-α-D-glucopyranosyl-(1→6)]- N^3-(4-amino-L-2-hydroxybutyryl)-2-deoxy-L-streptamine sulfate (1:2)

M.W. 585.61

The dosage form is supplied as a sterile, colorless to light straw colored solution for intramuscular or intravenous use. The 500 mg per 2 mL vial and 1 gram per 4 mL vial contains per each mL: 250 mg Amikacin (as the Amikacin sulfate USP), 0.66% sodium metabisulfite as an antioxidant, 2.5% sodium citrate dihydrate as a buffering agent with pH adjusted to 4.5 with sulfuric acid.

CLINICAL PHARMACOLOGY

Intramuscular Administration

Amikacin is rapidly absorbed after intramuscular administration. In normal adult volunteers, average peak serum concentrations of about 12, 16, and 21 mcg/mL are obtained 1 hour after intramuscular administration of 250 mg (3.7 mg/kg), 375 mg (5 mg/kg), 500 mg (7.5 mg/kg), single doses, respectively. At 10 hours, serum levels are about 0.3 mcg/mL, 1.2 mcg/mL, and 2.1 mcg/mL, respectively.

Tolerance studies in normal volunteers reveal that amikacin is well tolerated locally following repeated intramuscular dosing, and when given at maximally recommended doses, no ototoxicity or nephrotoxicity has been reported. There is no evidence of drug accumulation with repeated dosing for 10 days when administered according to recommended doses.

With normal renal function, about 91.9% of an intramuscular dose is excreted unchanged in the urine in the first 8 hours, and 98.2% within 24 hours. Mean urine concentrations for 6 hours are 563 mcg/mL following a 250 mg dose, 697 mcg/mL following a 375 mg dose, and 832 mcg/mL following a 500 mg dose.

Preliminary intramuscular studies in newborns of different weights (less than 1.5 kg, 1.5 to 2 kg, over 2 kg) at a dose of 7.5 mg/kg revealed that, like other aminoglycosides, serum half-life values were correlated inversely with post-natal age and renal clearances of amikacin. The volume of distribution indicates that amikacin, like other aminoglycosides, remains primarily in the extracellular fluid space of neonates. Repeated dosing every 12 hours in all the above groups did not demonstrate accumulation after 5 days.

Intravenous Administration

Single doses of 500 mg (7.5 mg/kg) administered to normal adults as an infusion over a period of 30 minutes produced a mean peak serum concentration of 38 mcg/mL at the end of the infusion, and levels of 24 mcg/mL, 18 mcg/mL, and 0.75 mcg/mL at 30 minutes, 1 hour, and 10 hours post-infusion, respectively. Eighty-four percent of the administered dose was excreted in the urine in 9 hours and about 94% within 24 hours. Repeat infusions of 7.5 mg/kg every 12 hours in normal adults were well tolerated and caused no drug accumulation.

General

Pharmacokinetic studies in normal adult subjects reveal the mean serum half-life to be slightly over 2 hours with a mean total apparent volume of distribution of 24 liters (28% of the body weight). By the ultrafiltration technique, reports of serum protein binding range from 0 to 11%. The mean serum clearance rate is about 100 mL/min and the renal clearance rate is 94 mL/min in subjects with normal renal function.

Amikacin is excreted primarily by glomerular filtration. Patients with impaired renal function or diminished glomerular filtration pressure excrete the drug much more slowly (effectively prolonging the serum half-life). Therefore, renal function should be monitored carefully and dosage adjusted accordingly (see suggested dosage scheduleunder DOSAGE AND ADMINISTRATION)

Following administration at the recommended dose, therapeutic levels are found in bone, heart, gallbladder, and lung tissue in addition to significant concentrations in urine, bile, sputum, bronchial secretions, interstitial, pleural, and synovial fluids.

Spinal fluid levels in normal infants are approximately 10 to 20% of the serum concentrations and may reach 50% when the meninges are inflamed. Amikacin has been demonstrated to cross the placental barrier and yield significant concentrations in amniotic fluid. The peak fetal serum concentration is about 16% of the peak maternal serum concentration and maternal and fetal serum half-life values are about 2 and 3.7 hours, respectively.

Microbiology

Mechanism of Action

Amikacin, an aminoglycoside, binds to the prokaryotic ribosome, inhibiting protein synthesis in susceptible bacteria. It is bactericidal in vitroagainst Gram-positive and Gram-negative bacteria.

Mechanism of Resistance

Aminoglycosides are known to be ineffective against Salmonellaand Shigellaspecies in patients. Therefore, in vitrosusceptibility test results should not be reported.

Amikacin resists degradation by certain aminoglycoside inactivating enzymes known to affect gentamicin, tobramycin, and kanamycin.

Aminoglycosides in general have a low order of activity against Gram-positive organisms other than Staphylococcalisolates.

Interaction with Other Antimicrobials

In vitrostudies have shown that amikacin sulfate combined with a beta-lactam antibiotic acts synergistically against many clinically significant Gram-negative organisms.

Antimicrobial Activity

Amikacin has been shown to be active against the following bacteria, both in vitroand in clinical infections [see Indications and Usage]

Gram-positive Bacteria

Staphylococcusspecies

Gram-negative Bacteria

Pseudomonasspecies

Escherichia coli

Proteusspecies (indole-positive and indole-negative)

Klebsiellaspecies

Enterobacterspecies

Serratiaspecies

Acinetobacterspecies

Amikacin has demonstrated in vitroactivity against the following bacteria. The safety and effectiveness of amikacin in treating clinical infections due to these bacteria have not been established in adequate and well-controlled trials.

Citrobacter freundii

Susceptibility Testing

For specific information regarding susceptibility test interpretive criteria and associated test methods and quality control standards recognized by FDA for this drug, please see: https://www.fda.gov/STIC.

INDICATIONS AND USAGE

Amikacin Sulfate Injection is indicated in the short-term treatment of serious infections due to susceptible strains of Gram-negative bacteria, including Pseudomonasspecies, Escherichia coli, species of indole-positive and indole-negative Proteus, Providenciaspecies, Klebsiella-Enterobacter-Serratiaspecies, and Acinetobacter(Mima-Herellea) species.

Clinical studies have shown Amikacin Sulfate Injection to be effective in bacterial septicemia (including neonatal sepsis); in serious infections of the respiratory tract, bones and joints, central nervous system (including meningitis) and skin and soft tissue; intra-abdominal infections (including peritonitis); and in burns and post-operative infections (including post-vascular surgery). Clinical studies have shown amikacin also to be effective in serious complicated and recurrent urinary tract infections due to these organisms. Aminoglycosides, including Amikacin Sulfate Injection are not indicated in uncomplicated initial episodes of urinary tract infections unless the causative organisms are not susceptible to antibiotics having less potential toxicity.

Bacteriologic studies should be performed to identify causative organisms and their susceptibilities to amikacin. Amikacin may be considered as initial therapy in suspected Gram-negative infections and therapy may be instituted before obtaining the results of susceptibility testing. Clinical trials demonstrated that amikacin was effective in infections caused by gentamicin and/or tobramycin-resistant strains of Gram-negative organisms, particularly Proteus rettgeri, Providencia stuartii, Serratia marcescens, and Pseudomonas aeruginosa. The decision to continue therapy with the drug should be based on results of the susceptibility tests, the severity of the infection, the response of the patient and the important additional considerations contained in the WARNINGSbox above.

Amikacin has also been shown to be effective in staphylococcal infections and may be considered as initial therapy under certain conditions in the treatment of known or suspected staphylococcal disease such as, severe infections where the causative organism may be either a Gram-negative bacterium or a staphylococcus, infections due to susceptible strains of staphylococci in patients allergic to other antibiotics, and in mixed staphylococci/Gram-negative infections.

In certain severe infections such as neonatal sepsis, concomitant therapy with a penicillin-type drug may be indicated because of the possibility of infections due to Gram-positive organisms such as streptococci or pneumococci.

To reduce the development of drug-resistant bacteria and maintain the effectiveness of amikacin and other antibacterial drugs, amikacin should be used only to treat or prevent infections that are proven or strongly suspected to be caused by susceptible bacteria.

When culture and susceptibility information are available, they should be considered in selecting or modifying antibacterial therapy.

In the absence of such data, local epidemiology and susceptibility patterns may contribute to the empiric selection of therapy.

CONTRAINDICATIONS

A history of hypersensitivity to amikacin is a contraindication for its use. A history of hypersensitivity or serious toxic reactions to aminoglycosides may contraindicate the use of any other aminoglycoside because of the known cross-sensitivities of patients to drugs in this class.

WARNINGS

See WARNINGS boxabove.

Aminoglycosides can cause fetal harm when administered to a pregnant woman. Aminoglycosides cross the placenta and there have been several reports of total irreversible, bilateral congenital deafness in children whose mothers received streptomycin during pregnancy. Although serious side effects to the fetus or newborns have not been reported in the treatment of pregnant women with other aminoglycosides, the potential for harm exists. Reproduction studies of amikacin have been performed in rats and mice and revealed no evidence of impaired fertility or harm to the fetus due to amikacin. There are no well controlled studies in pregnant women, but investigational experience does not include any positive evidence of adverse effects to the fetus. If this drug is used during pregnancy, or if the patient becomes pregnant while taking this drug, the patient should be apprised of the potential hazard to the fetus.

Contains sodium metabisulfite, a sulfite that may cause allergic-type reactions including anaphylactic symptoms and life-threatening or less severe asthmatic episodes in certain susceptible people. The overall prevalence of sulfite sensitivity in the general population is unknown and probably low. Sulfite sensitivity is seen more frequently in asthmatic than nonasthmatic people.

Clostridium difficileassociated diarrhea (CDAD) has been reported with use of nearly all antibacterial agents, including Amikacin Sulfate Injection, and may range in severity from mild diarrhea to fatal colitis. Treatment with antibacterial agents alters the normal flora of the colon leading to overgrowth of C. difficile.

C. difficileproduces toxins A and B which contribute to the development of CDAD. Hypertoxin producing strains of C. difficilecause increased morbidity and mortality, as these infections can be refractory to antimicrobial therapy and may require colectomy. CDAD must be considered in all patients who present with diarrhea following antibiotic use. Careful medical history is necessary since CDAD has been reported to occur over two months after the administration of antibacterial agents.

If CDAD is suspected or confirmed, ongoing antibiotic use not directed against C. difficilemay need to be discontinued. Appropriate fluid and electrolyte management, protein supplementation, antibiotic treatment of C. difficile, and surgical evaluation should be instituted as clinically indicated.

Risk of Ototoxicity Due to Mitochondrial DNA Variants

Cases of ototoxicity with aminoglycosides have been observed in patients with certain variants in the mitochondrially encoded 12S rRNA gene (MT-RNR1), particularly the m.1555A>G variant. Ototoxicity occurred in some patients even when their aminoglycoside serum levels were within the recommended range. Mitochondrial DNA variants are present in less than 1% of the general US population, and the proportion of the variant carriers who may develop ototoxicity as well as the severity of ototoxicity is unknown. In case of known maternal history of ototoxicity due to aminoglycoside use or a known mitochondrial DNA variant in the patient, consider alternative treatments other than aminoglycosides unless the increased risk of permanent hearing loss is outweighed by the severity of infection and lack of safe and effective alternative therapies.

PRECAUTIONS

General

Prescribing amikacin in the absence of a proven or strongly suspected bacterial infection or a prophylactic indication is unlikely to provide benefit to the patient and increases the risk of the development of drug-resistant bacteria.

Aminoglycosides are quickly and almost totally absorbed when they are applied topically, except to the urinary bladder, in association with surgical procedures. Irreversible deafness, renal failure, and death due to neuromuscular blockade have been reported following irrigation of both small and large surgical fields with an aminoglycoside preparation.

Amikacin Sulfate Injection is potentially nephrotoxic, ototoxic and neurotoxic. The concurrent or serial use of other ototoxic or nephrotoxic agents should be avoided either systemically or topically because of the potential for additive effects. Increased nephrotoxicity has been reported following concomitant parenteral administration of aminoglycoside antibiotics and cephalosporins.

Concomitant cephalosporins may spuriously elevate creatinine determinations.

Since amikacin is present in high concentrations in the renal excretory system, patients should be well hydrated to minimize chemical irritation of the renal tubules. Kidney function should be assessed by the usual methods prior to starting therapy and daily during the course of treatment. If signs of renal irritation appear (casts, white or red cells, or albumin), hydration should be increased. A reduction in dosage (see DOSAGE AND ADMINISTRATION) may be desirable if other evidence of renal dysfunction occurs such as decreased creatinine clearance; decreased urine specific gravity; increased BUN, creatinine, or oliguria. If azotemia increases or if a progressive decrease in urinary output occurs, treatment should be stopped.

Note: When patients are well-hydrated and kidney function is normal the risk of nephrotoxic reactions with amikacin is low if the dosage recommendations (see DOSAGE AND ADMINISTRATION) are not exceeded.

Elderly patients may have reduced renal function which may not be evident in routine screening tests such as BUN or serum creatinine. A creatinine clearance determination may be more useful. Monitoring of renal function during treatment with aminoglycosides is particularly important. Aminoglycosides should be used with caution in patients with muscular disorders such as myasthenia gravis or parkinsonism since these drugs may aggravate muscle weakness because of their potential curare-like effect on the neuromuscular junction.

In vitromixing of aminoglycosides with beta-lactam antibiotics (penicillin or cephalosporin) may result in a significant mutual inactivation. A reduction in serum half-life or serum level may occur when an aminoglycoside or penicillin-type drug is administered by separate routes. Inactivation of the aminoglycoside is clinically significant only in patients with severely impaired renal function. Inactivation may continue in specimens of body fluids collected for assay, resulting in inaccurate aminoglycoside readings. Such specimens should be properly handled (assayed promptly, frozen, or treated with beta-lactamase).

Cross-allergenicity among aminoglycosides has been demonstrated.

As with other antibiotics, the use of amikacin may result in overgrowth of nonsusceptible organisms. If this occurs, appropriate therapy should be instituted.

Aminoglycosides should not be given concurrently with potent diuretics (see WARNINGS box).

Information for Patients

Patients should be counseled that antibacterial drugs including amikacin should only be used to treat bacterial infections. They do not treat viral infections (e.g., the common cold). When amikacin is prescribed to treat a bacterial infection, patients should be told that although it is common to feel better early in the course of therapy, the medication should be taken exactly as directed. Skipping doses or not completing the full course of therapy may (1) decrease the effectiveness of the immediate treatment and (2) increase the likelihood that bacteria will develop resistance and will not be treatable by amikacin or other antibacterial drugs in the future.

Diarrhea is a common problem caused by antibiotics which usually ends when the antibiotic is discontinued. Sometimes after starting treatment with antibiotics, patients can develop watery and bloody stools (with or without stomach cramps and fever) even as late as two or more months after having taken the last dose of the antibiotic. If this occurs, patients should contact their physician as soon as possible.

Carcinogenesis, Mutagenesis, Impairment of Fertility

Long term studies in animals to evaluate carcinogenic potential have not been performed, and mutagenicity has not been studied. Amikacin administered subcutaneously to rats at doses up to 4 times the human daily dose did not impair male or female fertility.

Pregnancy

Teratogenic Effects

(See WARNINGSsection.)

Nursing Mothers

It is not known whether amikacin is excreted in human milk. Because many drugs are excreted in human milk and because of the potential for serious adverse reactions in nursing infants from amikacin, a decision should be made whether to discontinue nursing or to discontinue the drug, taking into account the importance of the drug to the mother.

Pediatric Use

Aminoglycosides should be used with caution in premature and neonatal infants because of the renal immaturity of these patients and the resulting prolongation of serum half-life of these drugs.

ADVERSE REACTIONS

All aminoglycosides have the potential to induce auditory, vestibular, and renal toxicity and neuromuscular blockade (see WARNINGS box). They occur more frequently in patients with present or past history of renal impairment, of treatment with other ototoxic or nephrotoxic drugs, and in patients treated for longer periods and/or with higher doses than recommended.

Neurotoxicity-Ototoxicity

Toxic effects on the eighth cranial nerve can result in hearing loss, loss of balance, or both. Amikacin primarily affects auditory function. Cochlear damage includes high frequency deafness and usually occurs before clinical hearing loss can be detected.

Neurotoxicity-Neuromuscular Blockade

Acute muscular paralysis and apnea can occur following treatment with aminoglycoside drugs.

Nephrotoxicity

Elevation of serum creatinine, albuminuria, presence of red and white cells, casts, azotemia, and oliguria have been reported. Renal function changes are usually reversible when the drug is discontinued. As would be expected with any aminoglycoside, reports of toxic nephropathy and acute renal failure have been received during postmarketing surveillance.

Other

In addition to those described above, other adverse reactions which have been reported on rare occasions are skin rash, drug fever, headache, paresthesia, tremor, nausea and vomiting, eosinophilia, arthralgia, anemia, hypotension and hypomagnesemia. Macular infarction sometimes leading to permanent loss of vision has been reported following intravitreous administration (injection into the eye) of amikacin.

To report SUSPECTED ADVERSE EVENTS, contact Mullan Pharmaceutical Inc. at +1-800-673-9839 or FDA at 1-800-FDA-1088 or www.fda.gov/medwatch.

OVERDOSAGE

In the event of overdosage or toxic reaction, peritoneal dialysis or hemodialysis will aid in the removal of amikacin from the blood. In the newborn infant, exchange transfusion may also be considered.

DOSAGE AND ADMINISTRATION

The patient's pretreatment body weight should be obtained for calculation of correct dosage. Amikacin Sulfate Injection may be given intramuscularly or intravenously.

The status of renal function should be estimated by measurement of the serum creatinine concentration or calculation of the endogenous creatinine clearance rate.

The blood urea nitrogen (BUN) is much less reliable for this purpose. Reassessment of renal function should be made periodically during therapy. Whenever possible, amikacin concentrations in serum should be measured to assure adequate but not excessive levels. It is desirable to measure both peak and trough serum concentrations intermittently during therapy. Peak concentrations (30 to 90 minutes after injection) above 35 micrograms per mL and trough concentrations (just prior to the next dose) above 10 micrograms per mL should be avoided. Dosage should be adjusted as indicated.

Since the vials are for single-dose only, any unused portion remaining in the vial should be discarded.

Intramuscular Administration for Patients with Normal Renal Function

The recommended dosage for adults, children and older infants (see WARNINGS box) with normal renal function is 15 mg/kg/day divided into 2 or 3 equal doses administered at equally-divided intervals, i.e., 7.5 mg/kg q12h or 5 mg/kg q8h. Treatment of patients in the heavier weight classes should not exceed 1.5 gram/day.

When amikacin is indicated in newborns (see WARNINGS box), it is recommended that a loading dose of 10 mg/kg be administered initially to be followed with 7.5 mg/kg every 12 hours.

The usual duration of treatment is 7 to 10 days. It is desirable to limit the duration of treatment to short term whenever feasible.

The total daily dose by all routes of administration should not exceed 15 mg/kg/day. In difficult and complicated infections where treatment beyond 10 days is considered, the use of amikacin should be reevaluated. If continued, amikacin serum levels, and renal, auditory, and vestibular functions should be monitored. At the recommended dosage level, uncomplicated infections due to amikacin-sensitive organisms should respond in 24 to 48 hours. If definite clinical response does not occur within 3 to 5 days, therapy should be stopped and the antibiotic susceptibility pattern of the invading organism should be rechecked. Failure of the infection to respond may be due to resistance of the organism or to the presence of septic foci requiring surgical drainage. When amikacin is indicated in uncomplicated urinary tract infections, a dose of 250 mg twice daily may be used.

DOSAGE GUIDELINES
ADULTS AND CHILDREN WITH NORMAL RENAL FUNCTION
Patient Weight |  | Dosage
lbs | kg | 7.5 mg/kg |  | 5 mg/kg
lbs | kg | q12h |  | q8h
99 | 45 | 337.5 mg | OR | 225 mg
110 | 50 | 375 mg | OR | 250 mg
121 | 55 | 412.5 mg | OR | 275 mg
132 | 60 | 450 mg | OR | 300 mg
143 | 65 | 487.5 mg | OR | 325 mg
154 | 70 | 525 mg | OR | 350 mg
165 | 75 | 562.5 mg | OR | 375 mg
176 | 80 | 600 mg | OR | 400 mg
187 | 85 | 637.5 mg | OR | 425 mg
198 | 90 | 675 mg | OR | 450 mg
209 | 95 | 712.5 mg | OR | 475 mg
220 | 100 | 750 mg | OR | 500 mg

Intramuscular Administration for Patients with Impaired Renal Function

Whenever possible, serum amikacin concentrations should be monitored by appropriate assay procedures. Doses may be adjusted in patients with impaired renal function either by administering normal doses at prolonged intervals or by administering reduced doses at a fixed interval.

Both methods are based on the patient's creatinine clearance or serum creatinine values since these have been found to correlate with aminoglycoside half-lives in patients with diminished renal function. These dosage schedules must be used in conjunction with careful clinical and laboratory observations of the patient and should be modified as necessary. Neither method should be used when dialysis is being performed.

Normal Dosage at Prolonged Intervals

If the creatinine clearance rate is not available and the patient's condition is stable, a dosage interval in hours for the normal dose can be calculated by multiplying the patient's serum creatinine by 9, e.g., if the serum creatinine concentration is 2 mg/100 mL, the recommended single dose (7.5 mg/kg) should be administered every 18 hours.

Reduced Dosage at Fixed Time Intervals

When renal function is impaired and it is desirable to administer amikacin at a fixed time interval, dosage must be reduced. In these patients, serum amikacin concentrations should be measured to assure accurate administration of amikacin and to avoid concentrations above 35 mcg/mL. If serum assay determinations are not available and the patient's condition is stable, serum creatinine and creatinine clearance values are the most readily available indicators of the degree of renal impairment to use as a guide for dosage.

First, initiate therapy by administering a normal dose, 7.5 mg/kg, as a loading dose. This loading dose is the same as the normally recommended dose which would be calculated for a patient with a normal renal function as described above.

To determine the size of maintenance doses administered every 12 hours, the loading dose should be reduced in proportion to the reduction in the patient's creatinine clearance rate:

Maintenance Dose Every 12 Hours | = | observed CC in mL/min ----------------------------- normal CC in mL/min | × | calculate loading dose in mg
(CC-creatinine clearance rate)

An alternate rough guide for determining reduced dosage at 12-hour intervals (for patients whose steady state serum creatinine values are known) is to divide the normally recommended dose by the patient's serum creatinine.

The above dosage schedules are not intended to be rigid recommendations but are provided as guides to dosage when the measurement of amikacin serum levels is not feasible.

Intravenous Administration

The individual dose, the total daily dose, and the total cumulative dose of amikacin sulfate are identical to the dose recommended for intramuscular administration. The solution for intravenous use is prepared by adding the contents of a 500 mg vial to 100 or 200 mL of sterile diluent such as 0.9% sodium chloride injection or 5% dextrose injection or any of the compatible solutions listed below.

The solution is administered to adults over a 30 to 60 minute period. The total daily dose should not exceed 15 mg/kg/day and may be divided into either 2 or 3 equally-divided doses at equally-divided intervals.

In pediatric patients the amount of fluid used will depend on the amount of amikacin ordered for the patient. It should be a sufficient amount to infuse the Amikacin Sulfate Injection over a 30 to 60 minute period. Infants should receive a 1 to 2 hour infusion.

Amikacin should not be physically premixed with other drugs but should be administered separately according to the recommended dose and route.

Stability in IV Fluids

Amikacin sulfate is stable for 24 hours at room temperature at concentrations of 0.25 and 5 mg/mL in the following solutions:

5% Dextrose Injection

5% Dextrose and 0.2% Sodium Chloride Injection

5% Dextrose and 0.45% Sodium Chloride Injection

0.9% Sodium Chloride Injection

Lactated Ringer's Injection

Normosol®M in 5% Dextrose Injection (or Plasma-Lyte 56 Injection in 5% Dextrose in Water)

Normosol®R in 5% Dextrose Injection (or Plasma-Lyte 148 Injection in 5% Dextrose in Water)

In the above solutions with Amikacin Sulfate Injection concentrations of 0.25 and 5 mg/mL, solutions aged for 60 days at 4°C and then stored at 25°C had utility times of 24 hours.

At the same concentrations, solutions frozen and aged for 30 days at - 15°C, thawed, and stored at 25°C had utility times of 24 hours. Parenteral drug products should be inspected visually for particulate matter and discoloration prior to administration whenever solution and container permit. Aminoglycosides administered by any of the above routes should not be physically premixed with other drugs but should be administered separately. Because of the potential toxicity of aminoglycosides, "fixed dosage" recommendations which are not based upon body weight are not advised. Rather, it is essential to calculate the dosage to fit the needs of each patient.

HOW SUPPLIED

Amikacin Sulfate Injection USP, 250 mg/mL is supplied as a clear colorless to light straw colored solution which requires no refrigeration. At times the solution may become a very pale yellow; this does not indicate a decrease in potency.

Amikacin Sulfate Injection USP, 250 mg/mL

Strength | NDC | Packing configuration
500 mg per 2 mL | 83301-0022-2 | 10 Single-Dose Vials (NDC 83301-0022-1) in a carton
1 gram per 4 mL | 83301-0023-2 | 10 Single-Dose Vials (NDC 83301-0023-1) in a carton

STORAGE AND HANDLING

Store at 20° to 25°C (68° to 77°F); excursions permitted between 15° to 30°C (59° to 86°F). [See USP Controlled Room Temperature].

Manufactured for:
Mullan Pharmaceutical Inc.Pasadena, CA 91101, USA
Manufactured by:
Qilu Pharmaceutical Co., Ltd.,Jinan, 250104, China

Revised: 04/2025

34040139911B

PRINCIPAL DISPLAY PANEL - 2 mL Vial Carton

NDC 83301-0022-2
Rx only

Amikacin Sulfate Injection, USP

Equivalent to Amikacin

500 mg/2 mL
(250 mg/mL)

For Intramuscular or Intravenous use

10 X 2 mL Single-Dose Vials

MULLAN
More choices for all

PRINCIPAL DISPLAY PANEL - 4 mL Vial Carton

NDC 83301-0023-2
Rx only

Amikacin Sulfate Injection, USP

Equivalent to Amikacin

1 gram/4 mL
(250 mg/mL)

For Intramuscular or Intravenous use

10 X 4 mL Single-Dose Vials

MULLAN
More choices for all